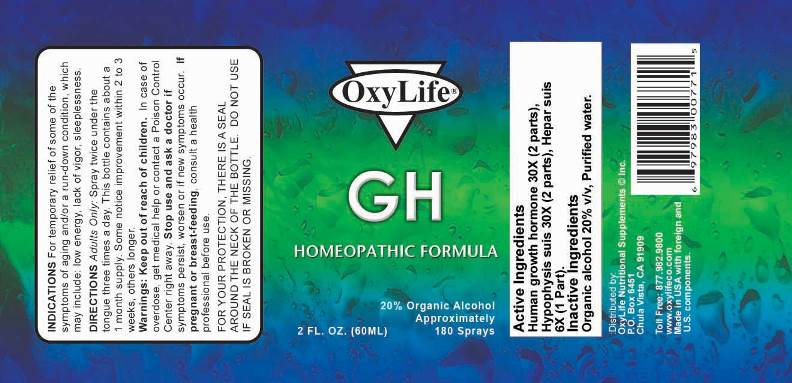 DRUG LABEL: GH
NDC: 49295-0001 | Form: SPRAY
Manufacturer: Oxylife Nutritional Supplements Inc
Category: homeopathic | Type: HUMAN OTC DRUG LABEL
Date: 20170928

ACTIVE INGREDIENTS: SOMATROPIN 30 [hp_X]/1 mL; SUS SCROFA PITUITARY GLAND 30 [hp_X]/1 mL; PORK LIVER 6 [hp_X]/1 mL
INACTIVE INGREDIENTS: WATER; ALCOHOL

Drug Facts:

ACTIVE INGREDIENTS:

Human Growth Hormone 30X (2 parts), Pituitaria Glandula 30X (2 parts), Hepar Suis 6X (1 part).

INDICATIONS:

For temporary relief of some of the symptoms of aging and/or a run-down condition, which may include: low energy, lack of vigor, sleeplessness.

WARNINGS:

Keep out of reach of children. In case of overdose, get medical help or contact a Poison Control Center right away.

Stop use and ask a doctor if symptoms persist, worsen or if new symptoms occur.

If pregnant or breast-feeding, consult a health professional before use.

FOR YOUR PROTECTION, THERE IS A SEAL AROUND THE NECK OF THE BOTTLE. DO NOT USE IF SEAL IS BROKEN OR MISSING.

Keep out of reach of children. In case of overdose, get medical help or contact a Poison Control Center right away.

DIRECTIONS:

Adults Only: Spray twice under the tongue three times a day. This bottle contains about a 1 month supply. Some notice improvement within 2 to 3 weeks, others longer.

INDICATIONS:

For temporary relief of some of the symptoms of aging and/or a run-down condition, which may include: low energy, lack of vigor, sleeplessness.

INACTIVE INGREDIENTS:

Organic alcohol 20% v/v, Purified water.

QUESTIONS:

:Distributed by:

OxyLife Nutritional Supplements Inc.

P.O. Box 6451

Chula Vista, CA 91909

Toll Free: 877-982-9800 www.oxylifeco.com

Made in USA with foreign and U.S. components

PACKAGE LABEL DISPLAY:

OxyLife

GH

HOMEOPATHIC FORMULA

Approximately 180 sprays

2 FL OZ. (60 ml)